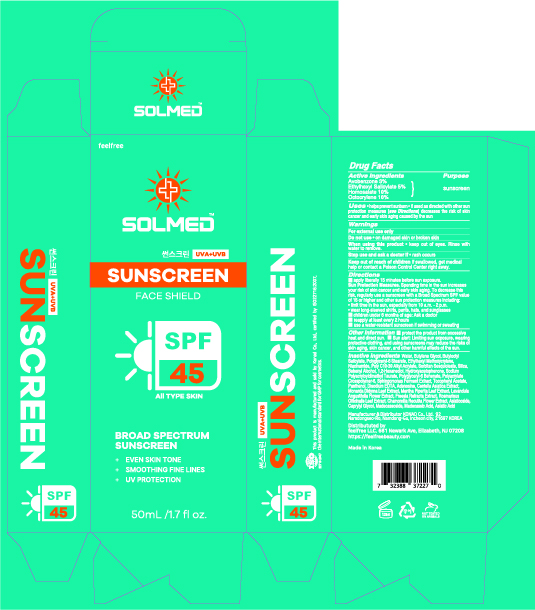 DRUG LABEL: SOLMED SUNSCREEN FACE SHIELD
NDC: 85446-045 | Form: CREAM
Manufacturer: FEELFREE LLC
Category: otc | Type: HUMAN OTC DRUG LABEL
Date: 20250331

ACTIVE INGREDIENTS: HOMOSALATE 5 g/50 g; ETHYLHEXYL SALICYLATE 2.5 g/50 g; AVOBENZONE 1.5 g/50 g; OCTOCRYLENE 5 g/50 g
INACTIVE INGREDIENTS: SODIUM POLYACRYLOYLDIMETHYL TAURATE; PANTHENOL; ASIATIC ACID; SORBITAN SESQUIOLEATE; POLYGLYCERYL-6 BEHENATE; POLYACRYLATE CROSSPOLYMER-6; EDETATE DISODIUM; WATER; ETHYLHEXYL METHOXYCRYLENE; 1,2-HEXANEDIOL; CENTELLA ASIATICA TRITERPENOIDS; MADECASSOSIDE; ADENOSINE; BUTYLENE GLYCOL; SILICA; BEHENYL ALCOHOL; HYDROXYACETOPHENONE; .ALPHA.-TOCOPHEROL ACETATE; MADECASSIC ACID; NIACINAMIDE; ROSEMARY; CAPRYLYL GLYCOL; BUTYLOCTYL SALICYLATE; POLYGLYCERYL-6 STEARATE; MONARDA DIDYMA LEAF; ASIATICOSIDE

SOLMED SUNSCREEN FACE SHIELD

Active ingredients

Avobenzone 3%

Ethylhexyl Salicylate 5%

Homosalate 10%
Octocrylene 10%

Purpose

sunscreen

Uses

• helps prevent sunburn • if used as directed with other sun protection measures (see Directions) decreases the risk of skin cancer and early skin aging caused by the sun

Warnings

For external use only

Do not use

• on damaged skin or broken skin

When using this product

• keep out of eyes. Rinse with water to remove.

Keep out of reach of children

If swallowed, get medical help or contact a Poison Control Center right away.

Directions

■ apply liberally 15 minutes before sun exposure.
Sun Protection Measures. Spending time in the sun increases your risk of skin cancer and early skin aging. To decrease this risk, regularly use a sunscreen with a Broad Spectrum SPF value of 15 or higher and other sun protection measures including:
• limit time in the sun, especially from 10 a.m. - 2 p.m.
• wear long-sleeved shirts, pants, hats, and sunglasses
■ children under 6 months of age: Ask a doctor
■ reapply at least every 2 hours
■ use a water-resistant sunscreen if swimming or sweating

Other information

■ protect the product from excessive heat and direct sun ■ Sun alert: Limiting sun exposure, wearing protective clothing, and using sunscreens may reduce the risks of skin aging, skin cancer, and other harmful effects of the sun.

Inactive ingredients

Water, Butylene Glycol, Butyloctyl Salicylate, Polyglyceryl-6 Stearate, Ethylhexyl Methoxycrylene, Niacinamide,

Poly C10-30 Alkyl Acrylate, Sorbitan Sesquioleate, Silica, Behenyl Alcohol, 1,2-Hexanediol, Hydroxyacetophenone,

Sodium Polyacryloyldimethyl Taurate, Polyglyceryl-6 Behenate, Polyacrylate Crosspolymer-6, Sphingomonas Ferment Extract, Tocopheryl Acetate, Panthenol, Disodium EDTA, Adenosine, Centella Asiatica Extract, Monarda Didyma Leaf Extract,

Mentha Piperita Leaf Extract, Lavandula Angustifolia Flower Extract, Freesia Refracta Extract, Rosmarinus Officinalis Leaf Extract, Chamomilla Recutita Flower Extract, Asiaticoside, Caprylyl Glycol, Madecassoside, Madecassic Acid, Asiatic Acid